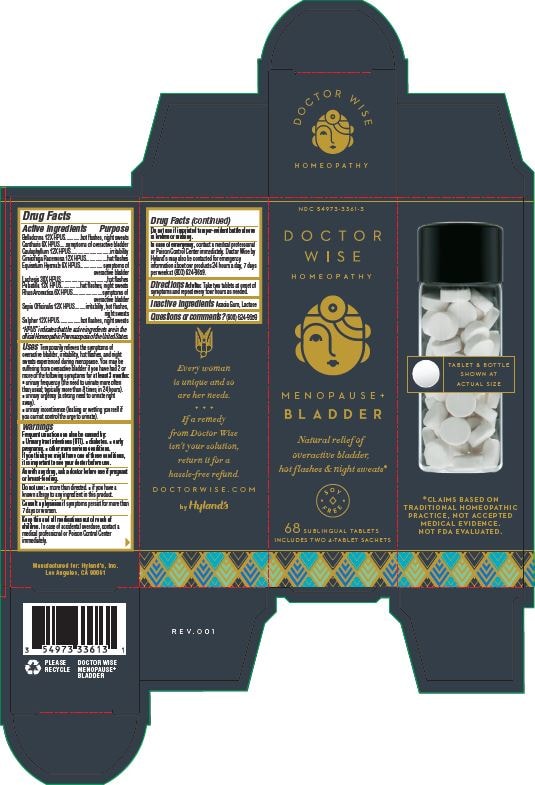 DRUG LABEL: Menopause Plus Bladder
NDC: 54973-3361 | Form: TABLET
Manufacturer: Hyland's Inc.
Category: homeopathic | Type: HUMAN OTC DRUG LABEL
Date: 20221212

ACTIVE INGREDIENTS: BLACK COHOSH 12 [hp_X]/1 1; ATROPA BELLADONNA 12 [hp_X]/1 1; SEPIA OFFICINALIS JUICE 12 [hp_X]/1 1; LACHESIS MUTA VENOM 30 [hp_X]/1 1; LYTTA VESICATORIA 6 [hp_X]/1 1; CAULOPHYLLUM THALICTROIDES ROOT 12 [hp_X]/1 1; EQUISETUM HYEMALE 6 [hp_X]/1 1; ANEMONE PULSATILLA 12 [hp_X]/1 1; RHUS AROMATICA ROOT BARK 6 [hp_X]/1 1; SULFUR 12 [hp_X]/1 1
INACTIVE INGREDIENTS: LACTOSE MONOHYDRATE; ACACIA

Doctor Wise Menopause + Bladder

Drug Facts

Active ingredients

Active ingredients | Purpose
Belladonna 12X HPUS | hot flashes, night sweats
Cantharis 6X HPUS | symptoms of overactive bladder
Caulophyllum 12X HPUS | irritability
Cimicifuga Racemosa 12X HPUS | hot flashes
Equisetum Hyemale 6X HPUS | symptoms of overactive bladder
Lachesis 30X HPUS | hot flashes
Pulsatilla 12X HPUS | hot flashes, night sweats
Rhus Aromatica 6X HPUS | symptoms of overactive bladder
Sepia Officinalis 12X HPUS | irritability, hot flashes, night sweats
Sulphur 12X HPUS | hot flashes, night sweats

“HPUS” indicates that the active ingredients are in the official Homeopathic Pharmacopœia of the United States.

Uses

Temporarily relieves the symptoms of overactive bladder, irritability, hot flashes, and night sweats experienced during menopause. You may be suffering from overactive bladder if you have had 2 or more of the following symptoms for at least 3 months:

• urinary frequency (the need to urinate more often than usual; typically more than 8 times in 24 hours).

• urinary urgency (a strong need to urinate right away).

• urinary incontinence (leaking or wetting yourself if you cannot control the urge to urinate).

Warnings

Frequent urination can also be caused by: • Urinary tract infections (UTI).  • diabetes.  • early pregnancy.  • other more serious conditions. If you think you might have one of these conditions, it is important to see your doctor before use.

PREGNANCY OR BREAST FEEDING

As with any drug, ask a doctor before use if pregnant or breast-feeding.

Do not use:  • more than directed.  • if you have a known allergy to any ingredient in this product.

ASK DOCTOR

Consult a physician if symptoms persist for more than 7 days or worsen.

KEEP OUT OF REACH OF CHILDREN

Keep this and all medications out of reach of children. In case of accidental overdose, contact a medical professional or Poison Control Center immediately.

Drug Facts (continued)

Do not use if imprinted tamper-evident bottle sleeve is broken or missing.

In case of emergency, contact a medical professional or Poison Control Center immediately. Doctor Wise by Hyland’s may also be contacted for emergency information about our products 24 hours a day, 7 days per week at (800) 624-9659.

Directions

Adults: Take two tablets at onset of symptoms and repeat every four hours as needed.

Inactive ingredients

Acacia Gum, Lactose

Questions or comments?

(800) 624-9659

Principal Display Panel - Menopause+ Bladder

NDC 54973-3361-3

DOCTOR

WISE

HOMEOPATHY

MENOPAUSE+

BLADDER

Natural relief of

overactive bladder,

hot flashes & night sweats*

SOY

FREE

68 SUBLINGUAL TABLETS

INCLUDES TWO 4-TABLET SACHETS